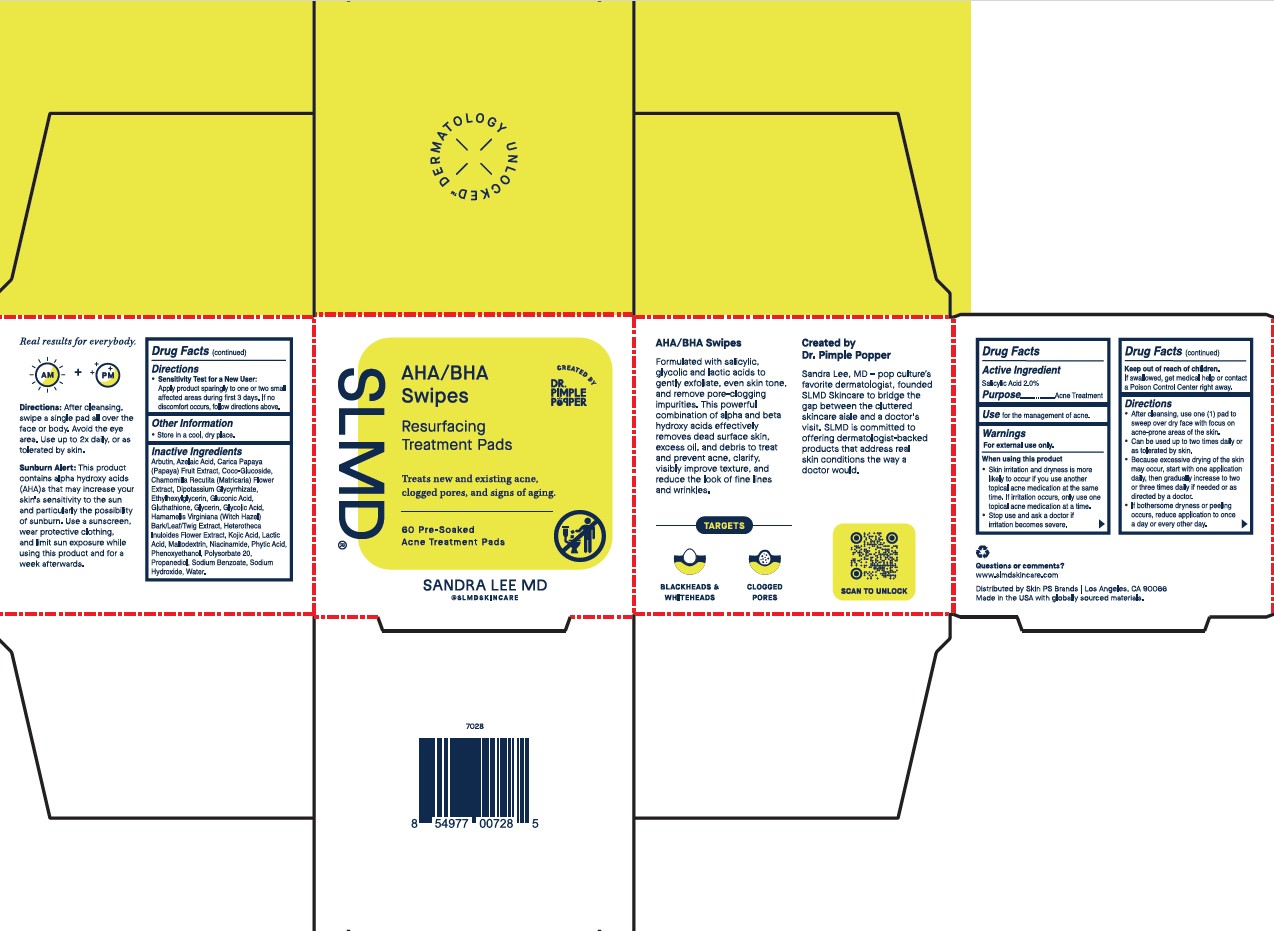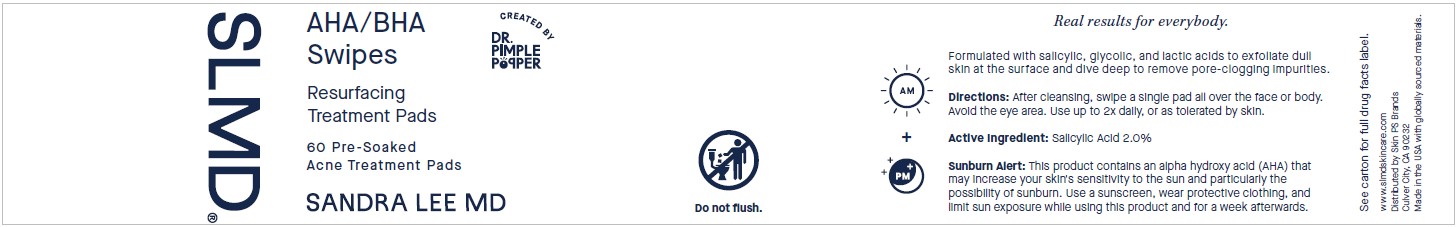 DRUG LABEL: Resurfacing acne swipes
NDC: 73318-4320 | Form: SWAB
Manufacturer: SKIN PS Brands
Category: otc | Type: HUMAN OTC DRUG LABEL
Date: 20260122

ACTIVE INGREDIENTS: SALICYLIC ACID 0.02 mg/1 mL
INACTIVE INGREDIENTS: POLYGLYCERYL-10 CAPRATE; KOJIC ACID; MALTODEXTRIN; POLYGLYCERYL-10 CAPRYLATE; GLYCERYL OLEATE; HAMAMELIS VIRGINIANA TOP; SODIUM HYDROXIDE; GLYCERIN; GLYCOLIC ACID; WATER; AZELAIC ACID; FYTIC ACID; GLYCYRRHIZINATE DIPOTASSIUM; GLUCONIC ACID; PHENOXYETHANOL; SODIUM BENZOATE; PROPANEDIOL; ARBUTIN; LACTIC ACID; DECYL GLUCOSIDE; GLUTATHIONE; ETHYLHEXYLGLYCERIN; NIACINAMIDE; PAPAYA; CHAMOMILE; HETEROTHECA INULOIDES FLOWER; CASTOR OIL; COCO GLUCOSIDE; POLYSORBATE 20

SLMD Resurfacing Acne Swipes

Active Ingredient

Salicylic Acid 2.0%

Purpose

Acne Treatment

Use

for the management of acne.

Warnings

For external use only.

When using this product

• Skin irritation and dryness is more likely to occur if you use another topical acne medication at the same time. If irritation occurs, only use one topical acne medication at a time.

• Stop use and ask a doctor if irriation becomes severe.

Keep out of reach of children

If swallowed, get medical help or contact a Poison Control Center right away.

Directions

• After cleansing, use one (1) pad to sweep over dry face with focus on acne-prone areas of the skin.

• Can be used up to two times daily or as tolerated by skin.

• Because excessive drying of the skin may occur, start with one application daily, then gradually increase to two or three times daily if needed or as directed by a doctor.

• If bothersome dryness or peeling occurs, reduce application to once a day or every other day.

• Sensitivity Test for a New User:

Apply product sparingly to one or two small affected areas during first 3 days. If no discomfort occurs, follow directions above.

Other information

• Store in a cool, dry place.

Inactive ingredients

Water, Sodium Hydroxide, Lactic Acid, Glycolic Acid, Phytic Acid, Polysorbate 20, Propanediol, Glycerin, Carica Papaya (Papaya) Fruit Extract, Chamomilla Recutita (Matricaria) Flower Extract, Hamamelis Virginiana (Witch Hazel) Bark/Leaf/Twig Extract, Heterotheca Inuloides Flower Extract, Ricinus Communis (Castor) Seed Oil, Decyl Glucoside, Coco-Glucoside, Polyglyceryl-10 Caprylate/Caprate, Arbutin, Azelaic Acid, Dipotassium Glycyrrhizate, Gluconic Acid, Glutathione, Glyceryl Oleate, Kojic Acid, Maltodextrin, Niacinamide, Phenoxyethanol, Ethylhexylglycerin, Sodium Benzoate.

Questions or comments?

slmdskincare.com

Label

DERMATOLOGY UNLOCKED™

SLMD®

AHA/BHA Swipes

Resurfacing Treatment Pads

Treats new and existing acne, clogged pores, and signs of aging.

60 Pre-soaked Acne Treatment Pads

CREATED BY DR. PIMPLE POPPER

SANDRA LEE MD

@SLMDSKINCARE

AHA/BHA Swipes

formulated with salicylic, glycolic and lactic acids to gently exfoliate, even skin tone, and remove pore-clogging impurities. This powerful combination of alpha and beta hydroxy acids surface skin, excess oil, and debris to treat and prevent acne, clarify, visibly improve texture, and reduce the look of fine lines and wrinkles.

----------TARGETS----------

BLACKHEADS & WHITEHEADS

CLOGGED PORES

Created by Dr. Pimple Popper

Sandra Lee, MD - pop culture's favorite dermatologist. founded SLMD Skincare to bridge the gap between the cluttered skincare aisle and a doctor's visit. SLMD is committed to offering dermatologist-backed products that address real skin conditions the way a doctor would.

SCAN TO UNLOCK

Drug Facts

Active Ingredient

Salicylic Acid 2.0%

Purpose…………… Acne Treatment

Use for the management of acne.

Warnings

For external use only.

When using this product

• Skin irritation and dryness is more likely to occur if you use another topical acne medication at the same time. If irritation occurs, only use one topical acne medication at a time.

• Stop use and ask a doctor if irritation becomes severe.

Keep out of reach of children.

If swallowed, get medical help or contact a Poison Control Center right away.

Directions

• After cleansing, use one (1) pad to sweep over dry face with focus on acne-prone areas of the skin.

• Can be used up to two times daily or as tolerated by skin.

• Because excessive drying of the skin may occur, start with one application daily, then gradually increase to two or three times daily if needed or as directed by a doctor.

• If bothersome dryness or peeling occurs, reduce application to once a day or every other day.

• Sensitivity Test for a New User:

Apply product sparingly to one or two small affected areas during first 3 days. If no discomfort occurs, follow directions above.

Other information

• Store in a cool, dry place.

Inactive ingredients

Water, Sodium Hydroxide, Lactic Acid, Glycolic Acid, Phytic Acid, Polysorbate 20, Propanediol, Glycerin, Carica Papaya (Papaya) Fruit Extract, Chamomilla Recutita (Matricaria) Flower Extract, Hamamelis Virginiana (Witch Hazel) Bark/Leaf/Twig Extract, Heterotheca Inuloides Flower Extract, Ricinus Communis (Castor) Seed Oil, Decyl Glucoside, Coco-Glucoside, Polyglyceryl-10 Caprylate/Caprate, Arbutin, Azelaic Acid, Dipotassium Glycyrrhizate, Gluconic Acid, Glutathione, Glyceryl Oleate, Kojic Acid, Maltodextrin, Niacinamide, Phenoxyethanol, Ethylhexylglycerin, Sodium Benzoate.

Questions or comments?

slmdskincare.com

Real results for everybody.

AM + PM

Directions: After cleansing, swipe a single pad all over the face or body. Avoid the eye area. Use up to 2 x daily, or as tolerated by skin.

Sunburn Alert: This product contains alpha hydroxy acids (AHA)s that may increase your skin's sensitivity to the sun and particularly the possibility of sunburn. use a sunscreen, wear protective clothing, and limit sun exposure while using this product and for a week afterwards.

www.slmdskincare.com

Distributed by Skin PS Brands

Culver City, CA 90232

Made in the USA with globally sourced materials.

7028

8 54977 00728 5

SLMD®

AHA/BHA Swipes

Resurfacing Treatment Pads

60 Pre-Soaked Acne Treatment Pads

SANDRA LEE MD

CREATED BY DR. PIMPLE POPPER

Do not flush.

AM + PM

Real results for everybody.

Formulated with salicylic, glycolic, and lactic acids to exfoliate dull skin at the surface and dive deep to remove pore-clogging impurities.

Directions: After cleansing, swipe a single pad all over the face or body. Avoid the eye area. Use up to 2x daily, or as tolerated by skin.

Active Ingredient: Salicylic Acid 2.0%

Sunburn Alert: This product contains an alpha hydroxy acid (AHA) that may increase your skin's sensitivity to the sun and particularly the possibility of sunburn. Use a sunscreen, wear protective clothing, and limit sun exposure while using this product and for a week afterwards.

See carton for full drug facts label.

www.slmdskincare.com

Distributed by Skin PS Brands

Culver City, CA 90232

Made in the USA with globally sourced materials.